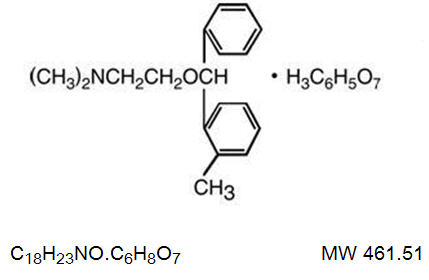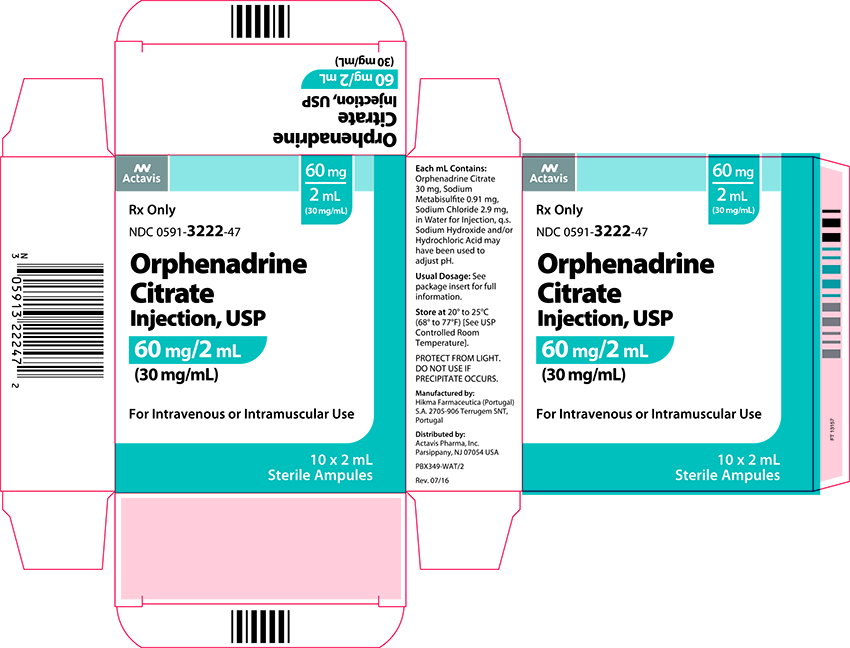 DRUG LABEL: Orphenadrine Citrate
NDC: 0591-3222 | Form: INJECTION
Manufacturer: Actavis Pharma, Inc.
Category: prescription | Type: HUMAN PRESCRIPTION DRUG LABEL
Date: 20160720

ACTIVE INGREDIENTS: ORPHENADRINE CITRATE 30 mg/1 mL
INACTIVE INGREDIENTS: SODIUM METABISULFITE 0.91 mg/1 mL; SODIUM CHLORIDE 2.9 mg/1 mL; WATER; SODIUM HYDROXIDE; HYDROCHLORIC ACID

ORPHENADRINE CITRATE INJECTION, USP
Rx Only

DESCRIPTION

Orphenadrine Citrate Injection is a sterile aqueous solution of orphenadrine citrate. It is intended for intravenous or intramuscular administration.

Orphenadrine citrate is the citrate salt of orphenadrine and occurs as a white, crystalline powder having a bitter taste. It is practically odorless, sparingly soluble in water and slightly soluble in alcohol. It has the following structural formula:

N,N-Dimethyl-2-[(o-methyl-α-phenylbenzyl)oxy]ethylamine Citrate (1:1).

Each mL contains: Orphenadrine Citrate 30 mg, Sodium Metabisulfite 0.91 mg, Sodium Chloride 2.9 mg, in Water for Injection q.s. Sodium Hydroxide and/or Hydrochloric Acid may have been used to adjust pH.

CLINICAL PHARMACOLOGY

The mode of action has not been clearly identified but may be related to analgesic properties. Orphenadrine citrate possesses anticholinergic actions.

INDICATIONS AND USAGE

Orphenadrine citrate is indicated as an adjunct to rest, physical therapy, and other measures for the relief of discomfort associated with acute, painful musculo-skeletal conditions. The mode of action of this drug has not been clearly identified, but may be related to its analgesic properties. Orphenadrine citrate does not directly relax tense skeletal muscles in man.

CONTRAINDICATIONS

Orphenadrine citrate is contraindicated in patients with glaucoma, pyloric or duodenal obstruction, stenosing peptic ulcers, prostatic hypertrophy or obstruction at the bladder neck, cardiospasm (megaesophagus) and myasthenia gravis.

Orphenadrine citrate is contraindicated in patients who have demonstrated a previous hypersensitivity to the drug.

WARNINGS

Contains Sodium Metabisulfite, a sulfite that may cause allergic-type reactions including anaphylactic symptoms and life-threatening or less severe asthmatic episodes in certain susceptible people. The overall prevalence of sulfite sensitivity in the general population is unknown and probably low. Sulfite sensitivity is seen more frequently in asthmatic than in nonasthmatic people.

Some patients may experience transient episodes of lightheadedness, dizziness or syncope.

Orphenadrine citrate may impair the ability of the patient to engage in potentially hazardous activities such as operating machinery or driving a motor vehicle; ambulatory patients should therefore be cautioned accordingly.

Usage in Pregnancy:

Safe use of orphenadrine citrate has not been established with respect to adverse effects upon fetal development. Therefore, orphenadrine citrate should be used in women of childbearing potential and particularly during early pregnancy only when in the judgment of the physician the potential benefits outweigh the possible hazards.

Usage in Children:

Safety and effectiveness in children have not been established; therefore, this drug is not recommended for use in the pediatric age group.

PRECAUTIONS

Confusion, anxiety and tremors have been reported in few patients receiving propoxyphene and orphenadrine concomitantly. As these symptoms may be simply due to an additive effect, reduction of dosage and/or discontinuation of one or both agents is recommended in such cases.

Orphenadrine citrate should be used with caution in patients with cardiac decompensation, coronary insufficiency, cardiac arrhythmias, and tachycardia.

Safety of continuous long term therapy with orphenadrine citrate has not been established. Therefore if orphenadrine citrate is prescribed for prolonged use, periodic monitoring of blood, urine, and liver function values is recommended.

ADVERSE REACTIONS

Adverse effects of orphenadrine citrate are mainly due to the mild anticholinergic action, and are usually associated with higher dosage. Dryness of the mouth is usually the first adverse effect to appear. When the daily dose is increased, possible adverse effects include: tachycardia, palpitation, urinary hesitancy or retention, blurred vision, dilatation of pupils, increased ocular tension, weakness, nausea, vomiting, headache, dizziness, constipation, drowsiness, hypersensitivity reactions, pruritus, hallucinations, agitation, tremor, gastric irritation, and rarely urticaria and other dermatoses. Infrequently, an elderly patient may experience some degree of mental confusion. These adverse reactions can usually be eliminated by reduction in dosage. Very rare cases of aplastic anemia associated with the use of orphenadrine tablets have been reported. No causal relationship has been established.

Rare instances of anaphylactic reaction have been reported associated with the intramuscular injection of orphenadrine citrate.

DOSAGE AND ADMINISTRATION

Adults: 2 mL (60 mg) intravenously or intramuscularly - May be repeated every 12 hours. Relief may be maintained by one (100 mg) orphenadrine citrate tablet twice daily.

Parenteral drug products should be inspected visually for particulate matter and discoloration prior to administration, whenever the solution and container permit.

HOW SUPPLIED

Orphenadrine Citrate Injection USP, 30 mg/mL is available in 2 mL ampules in cartons of 10.

Store at 20º to 25ºC (68º to 77ºF) [See USP Controlled Room Temperature.] PROTECT FROM LIGHT. DO NOT USE IF PRECIPITATE OCCURS.

Literature revised: July 2016

Product No.: 1108-82

Mfd. by: Hikma Farmaceutica
(Portugal) S.A. 2705-906 Terrugem SNT, Portugal

Dist. by: Actavis Pharma, Inc.
Parsippany, NJ 07054 USA

PRINCIPAL DISPLAY PANEL

Actavis

60 mg
2 mL
(30 mg/mL)

Rx Only

NDC 0591-3222-47

Orphenadrine
Citrate
Injection, USP

60 mg/2 mL
(30 mg/mL)

For Intravenous or Intramuscular Use
10 x 2 mL
Sterile Ampules